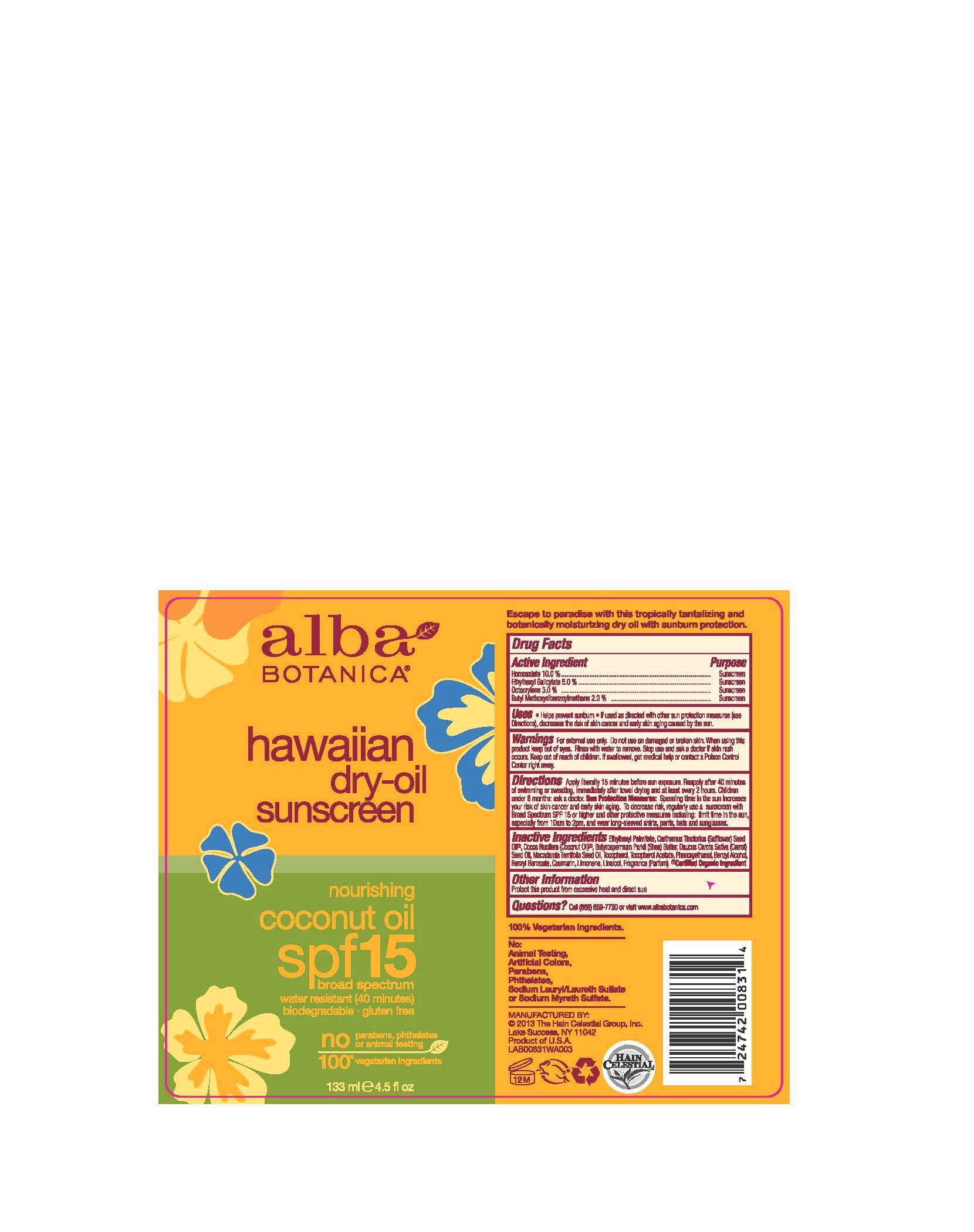 DRUG LABEL: Alba HawaiianDry Sunscreen SPF15
NDC: 61995-2102 | Form: OIL
Manufacturer: The Hain Celestial Group, Inc.
Category: otc | Type: HUMAN OTC DRUG LABEL
Date: 20140122

ACTIVE INGREDIENTS: HOMOSALATE 10.0 g/133 g; OCTISALATE 5.0 g/133 g; OCTOCRYLENE 3.0 g/133 g; AVOBENZONE 2.0 g/133 g
INACTIVE INGREDIENTS: ETHYLHEXYL PALMITATE; SAFFLOWER OIL; COCONUT OIL; SHEA BUTTER; CARROT SEED OIL; MACADAMIA OIL; TOCOPHEROL; .ALPHA.-TOCOPHEROL ACETATE; PHENOXYETHANOL

WARNINGS AND PRECAUTIONS

For external use only. do not use on damaged or broken skin. When using this product keep out of eyes. Rinse with water to remove. Stop use and ask a doctor if skin rash occurs.

Drug Facts

Homosalate 10%

Ethylhexyl Salicylate 5.0%

Octocrylene 3.0%

Butyl Methoxydibenzoylmethane 2.0%

Purpose: Sunscreen

Keep out of reach of children. If swallowed, get medical help or contact Poison Center right away.

OTHER SAFETY INFORMATION

Sun Protection Measures: Spending time

INACTIVE INGREDIENT

Ethylhexyl Palmitate, Carthamus Tinctorius (Safflower) Seed Oil (1), Cocos Nucifera (Coconut) Oil (1), Butyrospermum Parkii (Shea) Butter, Daucus Carota Sativa (Carrot) Seed Oil, Tocopherol, Tocopherol Acetate, Phenixyethanol, Fragrance.

(1) Certified Organic Ingredient